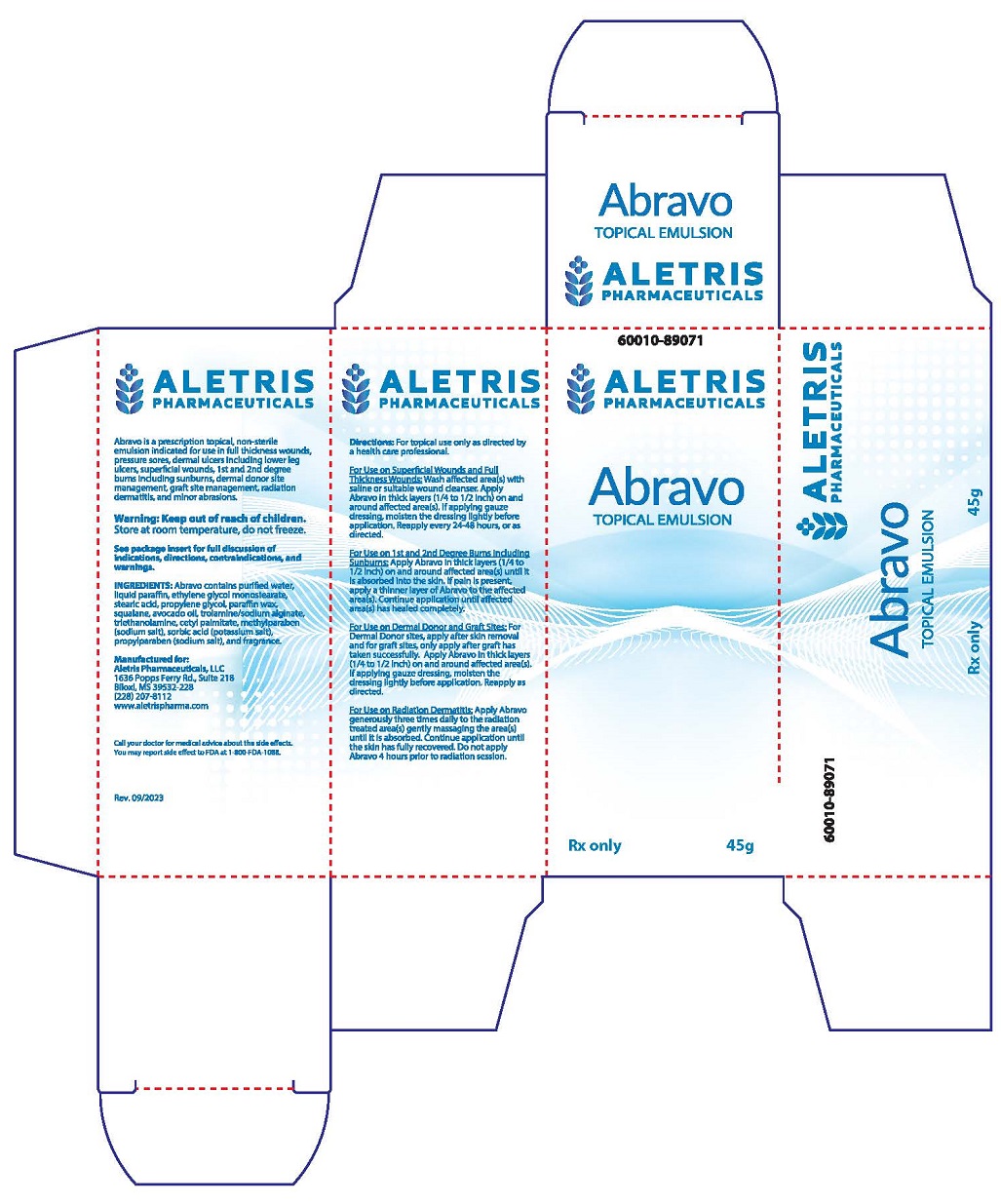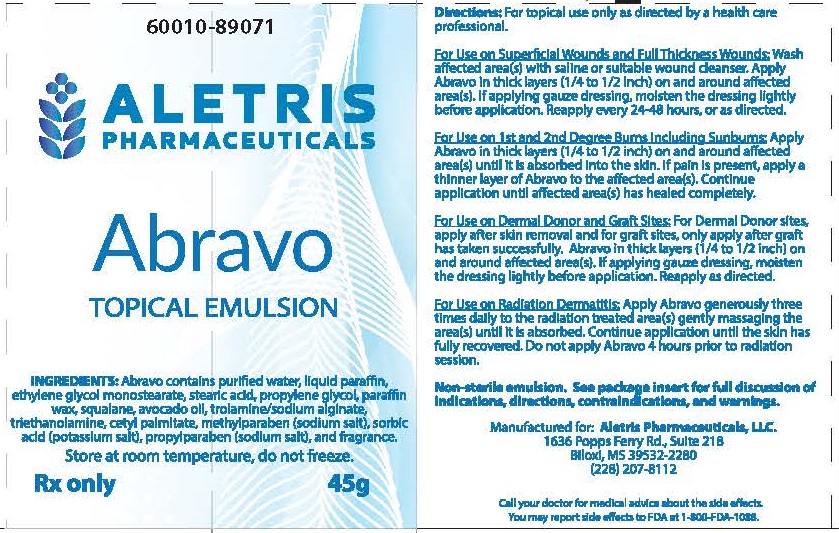 DRUG LABEL: Abravo Topical Emulsion
NDC: 86001089071
Manufacturer: Aletris Pharmaceuticals, LLC
Category: other | Type: PRESCRIPTION MEDICAL DEVICE LABEL
Date: 20231107

Abravo Topical Emulsion

TOPICAL EMULSION

Rx Only

DESCRIPTION

Abravo is a water-based, non-sterile emulsion formulated for the dressing and management of superficial wounds, minor abrasions, dermal ulcers, donor sites, 1st and 2nd degree burns, including sunburns, and radiation dermatitis. When applied properly to a wound, Abravo provides an optimum moist environment for the healing process and isolates the wound from harmful germs and other external contamination.

INDICATIONS AND USAGE

Abravo is indicated for use in:

- Full Thickness Wounds, Pressure Sores, Dermal Ulcers including Lower Leg Ulcers
- Superficial Wounds
- 1st and 2nd Degree Burns, including Sunburns
- Dermal Donor and Graft Site Management
- Radiation Dermatitis
- Minor Abrasions

CONTRAINDICATIONS

Abravo is contraindicated for use on bleeding wounds, skin rashes related to food or medicine allergies, and when an allergy to one of the ingredients is known.

WARNINGS

- In radiation therapy, Abravo may be applied as directed by the treating physician. Do not apply 4 hours prior to a radiation session.
- Do not apply Abravo to dermal grafts until after the graft has successfully taken.
- Do not apply to the eyes or to mucous membranes.
- Not for internal use.
- Keep out of reach of children.

Caution:

- For the treatment of any dermal wound, consult a physician. Use Abravo only as directed.
- Abravo is non-toxic, it is for topical use only and should not be ingested or taken internally.
- Abravo does not contain a sunscreen and should not be used prior to extended exposure to the sun.
- The use of Abravo on skin rashes due to allergies has not been studied sufficiently and therefore is not recommended.
- Following the application of Abravo a temporary tingling sensation may occur (10 to 15 minutes).
- If clinical signs of infection are present, appropriate treatment should be initiated. If clinically indicated, use of Abravo may be continued during the anti-infective therapy.
- If condition does not improve within 10-14 days, consult a physician.
- Abravo may dissolve fuchsin when this dye is used to define the margins of the radiation fields to be treated.

INSTRUCTIONS FOR USE

Abravo is for topical use only as directed by a healthcare professional.

Wounds, Abrasions, Full Thickness Wounds, Dermal Graft Site Management and Donor Site Management

- Wash the affected area(s) with saline, clean water, or a suitable wound cleanser.
- Apply Abravo on and around the affected area(s) in thick layers 1/4to 1/2 inch thick.
- If applying gauze dressing, moisten the dressing lightly before application.
- Reapply Abravo as described above every 24 to 48 hours or as directed until the wound or lesion has healed fully.
- For donor site management, apply Abravo after skin removal and cover with a moist dressing. Reapply as directed.
- For dermal graft site management, apply Abravo to the graft site only after the graft has taken successfully. Abravo can be washed away with a saline solution or clean water without causing damage to the newly formed tissues.

1st and 2nd Degree Burns, Including Sunburns

- Before application of Abravo to burns, take precaution in removing any clothing in the affected area(s).
- Apply Abravo as soon as possible on and around the affected area(s), in a thick 1/4 to 1/2 inch layer until the skin no longer absorbs the product. A white waxy residue may remain. If pain from the burn persists, apply thinner layers of Atopavo until the pain has ceased.
- Continue to apply Abravo until the affected areas(s) has healed completely.
- Application of Abravo to the affected area(s) should continue during any subsequent physical therapy treatments.

Radiation Dermatitis

- Apply a generous amount of Abravo three times per day, seven days a week to the treated area(s), gently massaging the area(s) until Abravo is completely absorbed.
- Abravo may be applied as indicated by the treating physician (see WARNINGS).
- Continue to apply Abravoas described above until the skin has fully recovered.
- Do not interrupt applications during the course of radiation therapy, even for one day.
- Do not apply Abravo 4 hours prior to a radiation session.

INACTIVE INGREDIENT

Abravo contains purified water, liquid paraffin, ethylene glycol monostearate, stearic acid, propylene glycol, paraffin wax, squalane, avocado oil, trolamine/sodium alginate, triethanolamine, cetyl palmitate, methylparaben (sodium salt), sorbic acid (potassium salt), propylparaben (sodium salt), and fragrance.

HOW SUPPLIED

Abravo is supplied in a 45-gram tube (60010-89071).
Store at room temperature, do not freeze.
Rx ONLY - Prescription Medical Device: Federal Law restricts this device to sale by or on the order of a physician (or properly licensed practitioner).

Manufactured for:
Aletris Pharmaceuticals, LLC.
1636 Popps Ferry Rd., Suite 218
Biloxi, MS 39532-2280
(228) 207-8112
www.aletrispharma.com

Call your doctor for medJcal advice about the side effects.
You may report side effects to FDA at 1-800-fDA-1088.